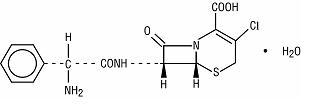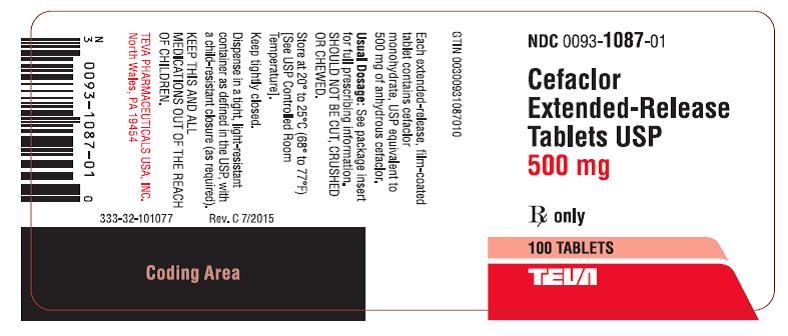 DRUG LABEL: Cefaclor
NDC: 0093-1087 | Form: TABLET, FILM COATED, EXTENDED RELEASE
Manufacturer: Teva Pharmaceuticals USA, Inc.
Category: prescription | Type: HUMAN PRESCRIPTION DRUG LABEL
Date: 20190731

ACTIVE INGREDIENTS: CEFACLOR 500 mg/1 1
INACTIVE INGREDIENTS: FD&C BLUE NO. 2; INDIGOTINDISULFONATE SODIUM; ALUMINUM OXIDE; HYPROMELLOSE 2208 (100 MPA.S); HYPROMELLOSE 2910 (6 MPA.S); MAGNESIUM STEARATE; MANNITOL; POLYETHYLENE GLYCOL 400; POVIDONE K30; TITANIUM DIOXIDE

CEFACLOR EXTENDED-RELEASE TABLETS USP
Rx only

To reduce the development of drug-resistant bacteria and maintain the effectiveness of cefaclor extended-release tablets USP and other antibacterial drugs, cefaclor extended-release tablets USP should be used only to treat or prevent infections that are proven or strongly suspected to be caused by bacteria.

DESCRIPTION

Cefaclor, USP, the active ingredient in cefaclor extended-release tablets USP, is a semisynthetic cephalosporin antibiotic for oral administration. Cefaclor, USP, is chemically designated as 3-chloro-7-D(2-phenylglycinamido)-3-cephem-4-carboxylic acid monohydrate. The cefaclor extended-release tablets formulation of cefaclor differs pharmacokinetically from the immediate-release formulation of cefaclor.

C15H14ClN3O4S • H2O M.W. 385.82

Each cefaclor extended-release tablet contains cefaclor monohydrate equivalent to 500 mg (1.36 mmol) anhydrous cefaclor. In addition, each extended-release tablet contains the following inactive ingredients: FD&C Blue #2 - indigo carmine lake, hypromellose, magnesium stearate, mannitol, polyethylene glycol, povidone and titanium dioxide.

CLINICAL PHARMACOLOGY

Pharmacokinetics

The cefaclor extended-release tablet formulation of cefaclor is pharmacokinetically different from the cefaclor immediate-release capsule formulation of cefaclor. (See TABLE 1.) No direct comparisons with the suspension formulation of cefaclor have been conducted; therefore, there are no data with which to compare the pharmacokinetic properties of the extended-release tablet formulation and the suspension formulation. Until further data are available, the pharmacokinetic equivalence of the extended-release tablet and the suspension formulations should NOT be assumed.

Absorption and Metabolism

The extent of absorption (AUC) and the maximum plasma concentration (Cmax) of cefaclor from cefaclor extended-release tablets are greater when the extended-release tablet is taken with food.

[NOTE: The extent of absorption (AUC) of cefaclor from cefaclor immediate-release capsules is unaffected by food intake; however, when cefaclor immediate-release capsules are taken with food, the Cmax is decreased.]

There is no evidence of metabolism of cefaclor in humans.

Comparative Serum Pharmacokinetics

Serum pharmacokinetic parameters for cefaclor extended-release tablets and cefaclor immediate-release capsules are shown in the table below.

Table 1: COMPARATIVE PHARMACOKINETICS OF CEFACLOR IMMEDIATE-RELEASE CAPSULES VS. CEFACLOR EXTENDED-RELEASE TABLETS IN FASTING AND FED STATES
Parameter | Cefaclor Extended-Release Tablets |  | Cefaclor Extended-Release Tablets |  | Cefaclor Immediate-Release Capsules
 | 375 mg |  | 500 mg |  | 2 x 250 mg
 | fed | fast | fed | fast | fed | fast
 | n = 10 |  | n = 16 | n = 16 | n = 15 | n = 16
Cmax | 3.7 (1.1) | NA | 8.2 (4.2) | 5.4 (1.6) | 9.3 (2.7) | 16.8 (4.7)
Tmax | 2.7 (1.0) | NA | 2.5 (0.8) | 1.5 (0.7) | 1.5 (0.6) | 0.9 (0.4)
AUC | 9.9 (2.2) | NA | 18.1 (4.2) | 14.8 (4.0) | 20.5 (2.8) | 19.2 (5.0)
(± 1 standard deviation)
NA = data not available

No drug accumulation was noted when cefaclor extended-release tablets were given twice daily.

The plasma half-life in healthy subjects is independent of dosage form and averages approximately 1 hour.

Food Effect on Pharmacokinetics

When cefaclor extended-release tablets are taken with food, the AUC is 10% lower while the Cmax is 12% lower and occurs 1 hour later compared to cefaclor immediate-release capsules. In contrast, when cefaclor extended-release tablets are taken without food, the AUC is 23% lower while the Cmax is 67% lower and occurs 0.6 hours later, using an equivalent milligram dose of cefaclor immediate-release capsules as a reference. Therefore, cefaclor extended-release tablets should be taken with food.

Special Populations

Renal Insufficiency

In patients with reduced renal function, the serum half-life of cefaclor is slightly prolonged. In those with complete absence of renal function, the plasma half-life of the intact molecule is 2.3 to 2.8 hours. Excretion pathways in patients with markedly impaired renal function have not been determined. Hemodialysis shortens the half-life by 25% to 30%.

Geriatric Patients

Healthy geriatric volunteers (≥ 65 years old) who received a single 750 mg dose of cefaclor extendedrelease tablets had 40%-50% higher AUC and 20% lower renal clearance values when compared to healthy adult volunteers less than 45 years of age. These differences are considered to be primarily a result of age-related decreases in renal function.

In elderly subjects (over age 65) with normal serum creatinine values, higher peak plasma concentrations and AUCs have been observed. This is considered to be primarily a result of an age-related decrement in renal function and has no apparent clinical significance. Therefore, dosage adjustment is not necessary in elderly subjects with normal serum creatinine values.

Microbiology

Mechanism of Action

As with other cephalosporins, the bactericidal action of cefaclor results from inhibition of cell-wall synthesis.

Mechanism of Resistance

Resistance to cefaclor is primarily through hydrolysis of ß-lactamases alteration of penicillin-binding proteins (PBPs) and decreased permeability. Pseudomonas spp., Acinetobacter calcoaceticus and most isolates of Enterococci (Enterococcus faecalis, group D streptococci), Enterobacter spp., indole-positive Proteus, Morganella morganii (formerly Proteus morganii), Providencia rettgeri (formerly Proteus rettgeri) and Serratia spp. are resistant to cefaclor. Cefaclor is inactive against methicillin-resistant staphylococci, ß-lactamase-negative, ampicillin-resistant isolates of H. influenzae should be considered resistant to cefaclor despite apparent in vitro susceptibility to this agent.

List of Microorganisms

Cefaclor has been shown to be active against most isolates of the following microorganisms both in vitro and in clinical infections as described in the INDICATIONS AND USAGE section.

Gram-positive Bacteria

Staphylococcus aureus (methicillin susceptible only)

Streptococcus pneumoniae

Streptococcus pyogenes

Gram-negative Bacteria

Haemophilus influenzae (excluding β-lactamase-negative, ampicillin-resistant isolates)

Moraxella catarrhalis

The following in vitro data are available, but their clinical significance is unknown. At least 90 percent of the following bacteria exhibit in vitro minimum inhibitory concentrations (MICs) less than or equal to the susceptible breakpoint for cefaclor against isolates of similar genus or organism group. However, the efficacy of cefaclor in treating clinical infections caused by these bacteria has not been established in adequate and well-controlled trials.

Gram-positive Bacteria

Staphylococcus epidermidis (methicillin susceptible only)

Gram-negative Bacteria

Haemophilus parainfluenzae

Klebsiella pneumoniae

Anaerobic Bacteria

Peptococcus niger

Peptostreptococci

Propionibacterium acnes

Susceptibility Testing

For specific information regarding susceptibility test interpretive criteria and associated test methods and quality control standards recognized by FDA for this drug, please see: https://www.fda.gov/STIC.

INDICATIONS AND USAGE

To reduce the development of drug-resistant bacteria and maintain the effectiveness of cefaclor extended-release tablets USP and other antibacterial drugs, cefaclor extended-release tablets USP should be used only to treat or prevent infections that are proven or strongly suspected to be caused by susceptible bacteria. When culture and susceptibility information are available, they should be considered in selecting or modifying antibacterial therapy. In the absence of such data, local epidemiology and susceptibility patterns may contribute to the empiric selection of therapy.

The safety and effectiveness of cefaclor extended-release tablets in treating some of the indications and pathogens for which other formulations of cefaclor are approved have NOT been established. When administered at the recommended dosages and durations of therapy, cefaclor extended-release tablets are indicated for the treatment of patients with the following mild to moderate infections when caused by susceptible strains of the designated organisms. (See DOSAGE AND ADMINISTRATION and CLINICAL STUDIES sections.)

Acute bacterial exacerbations of chronic bronchitis due to Haemophilus influenzae (excluding ß-lactamase-negative, ampicillin-resistant isolates), Moraxella catarrhalis, or Streptococcus pneumoniae.

NOTE: In view of the insufficient numbers of isolates of ß-lactamase-producing isolates of Haemophilus influenzae that were obtained from clinical trials with cefaclor extended-release tablets for patients with acute bacterial exacerbations of chronic bronchitis, it was not possible to adequately evaluate the effectiveness of cefaclor extended-release tablets for bronchitis known, suspected, or considered potentially to be caused by ß-lactamase-producing H. influenzae.

Pharyngitis and tonsillitis due to Streptococcus pyogenes.

NOTE: Only penicillin by the intramuscular route of administration has been shown to be effective in the prophylaxis of rheumatic fever. Cefaclor extended-release tablets are generally effective in the eradication of S. pyogenes from the oropharynx; however, data establishing the efficacy of cefaclor extended-release tablets for the prophylaxis of subsequent rheumatic fever are not available.

Uncomplicated skin and skin and structure infections due to Staphylococcus aureus (methicillin-susceptible only).

NOTE: In view of the insufficient numbers of isolates of Streptococcus pyogenes that were obtained from clinical trials with cefaclor extended-release tablets for patients with uncomplicated skin and skin structure infections, it was not possible to adequately evaluate the effectiveness of cefaclor extended-release tablets for skin infections known, suspected, or considered potentially to be caused by S. pyogenes.

CONTRAINDICATIONS

Cefaclor extended-release tablets are contraindicated in patients with known hypersensitivity to cefaclor and other cephalosporins.

WARNINGS

BEFORE THERAPY WITH CEFACLOR EXTENDED-RELEASE TABLETS IS INSTITUTED, CAREFUL INQUIRY SHOULD BE MADE TO DETERMINE WHETHER THE PATIENT HAS HAD PREVIOUS HYPERSENSITIVITY REACTIONS TO CEFACLOR, CEPHALOSPORINS, PENICILLINS, OR OTHER DRUGS. IF THIS PRODUCT IS TO BE GIVEN TO PENICILLIN-SENSITIVE PATIENTS, CAUTION SHOULD BE EXERCISED BECAUSE CROSS-SENSITIVITY AMONG BETA-LACTAM ANTIBIOTICS HAS BEEN CLEARLY DOCUMENTED AND MAY OCCUR IN UP TO 10% OF PATIENTS WITH A HISTORY OF PENICILLIN ALLERGY. IF AN ALLERGIC REACTION TO CEFACLOR EXTENDED-RELEASE TABLETS OCCURS, DISCONTINUE THE DRUG. SERIOUS ACUTE HYPERSENSITIVITY REACTIONS MAY REQUIRE TREATMENT WITH EPINEPHRINE AND OTHER EMERGENCY MEASURES, INCLUDING OXYGEN, INTRAVENOUS FLUIDS, INTRAVENOUS ANTIHISTAMINES, CORTICOSTEROIDS, PRESSOR AMINES, AND AIRWAY MANAGEMENT, AS CLINICALLY INDICATED.

Clostridium difficile associated diarrhea (CDAD) has been reported with use of nearly all antibacterial agents, including cefaclor and may range in severity from mild diarrhea to fatal colitis. Treatment with antibacterial agents alters the normal flora of the colon leading to overgrowth of C. difficile.

C. difficile produces toxins A and B which contribute to the development of CDAD. Hypertoxin producing strains of C. difficile cause increased morbidity and mortality, as these infections can be refractory to antimicrobial therapy and may require colectomy. CDAD must be considered in all patients who present with diarrhea following antibiotic use. Careful medical history is necessary since CDAD has been reported to occur over two months after the administration of antibacterial agents.

If CDAD is suspected or confirmed, ongoing antibiotic use not directed against C. difficile may need to be discontinued. Appropriate fluid and electrolyte management, protein supplementation, antibiotic treatment of C. difficile, and surgical evaluation should be instituted as clinically indicated.

PRECAUTIONS

General

Prescribing cefaclor extended-release tablets USP in the absence of a proven or strongly suspected bacterial infection or a prophylactic indication is unlikely to provide benefit to the patient and increases the risk of the development of drug-resistant bacteria.

Superinfection (overgrowth by non-susceptible organisms) should always be considered a possibility in a patient being treated with a broad spectrum antimicrobial. Careful observation of the patient is essential. If superinfection occurs during therapy, appropriate measures should be taken.

Information for Patients

Patients should be counseled that antibacterial drugs including cefaclor extended-release tablets USP should only be used to treat bacterial infections. They do not treat viral infections (e.g., the common cold). When cefaclor extended-release tablets USP are prescribed to treat a bacterial infection, patients should be told that although it is common to feel better early in the course of therapy, the medication should be taken exactly as directed. Skipping doses or not completing the full course of therapy may (1) decrease the effectiveness of the immediate treatment and (2) increase the likelihood that bacteria will develop resistance and will not be treatable by cefaclor extended-release tablets USP or other antibacterial drugs in the future.

Diarrhea is a common problem caused by antibiotics which usually ends when the antibiotic is discontinued. Sometimes after starting treatment with antibiotics, patients can develop watery and bloody stools (with or without stomach cramps and fever) even as late as two or more months after having taken the last dose of the antibiotic. If this occurs, patients should contact their physician as soon as possible.

Drug Interactions

Antacids

The extent of absorption of cefaclor extended-release tablets is diminished if magnesium or aluminum hydroxide-containing antacids are taken within 1 hour of administration; H2 blockers do not alter either the rate or the extent of absorption of cefaclor extended-release tablets.

Probenecid

The renal excretion of cefaclor is inhibited by probenecid.

Warfarin

There have been rare reports of increased prothrombin time with or without clinical bleeding in patients receiving cefaclor and warfarin concomitantly. No specific studies have been performed to rule in or rule out this potential drug/drug interaction.

Laboratory Test Interactions

Administration of cefaclor extended-release tablets may result in a false-positive reaction for glucose in the urine. This phenomenon has been seen in patients taking cephalosporin antibiotics when the test is performed using Benedict's and Fehling's solutions and also with Clinitest® tablets.

Carcinogenesis, Mutagenesis, Impairment of Fertility

Studies in animals have not been performed to evaluate the carcinogenic or mutagenic potential for cefaclor. Reproduction studies have revealed no evidence of impaired fertility.

Usage in Pregnancy

Teratogenic Effect

Reproduction studies using cefaclor have been performed in mice, rats and ferrets at doses up to 3 to 5 times the maximum human dose (1500 mg/day) based on mg/m^2. These studies have revealed no harm to the fetus due to cefaclor. There are, however, no adequate and well-controlled studies in pregnant women. Because animal reproduction studies are not always predictive of human response, cefaclor extended-release tablets should be used during pregnancy only if clearly needed.

Labor and Delivery

Cefaclor extended-release tablets have not been studied for use during labor and delivery. Treatment should be given only if clearly needed.

Nursing Mothers

No studies in lactating women have been performed with cefaclor extended-release tablets. Small amounts of cefaclor (≤ 0.21 mcg/mL) have been detected in human milk following administration of single 500 mg doses of cefaclor extended-release tablets. The effect on nursing infants is not known. Caution should be exercised when cefaclor extended-release tablets are administered to a nursing woman.

Pediatric Use

Safety and effectiveness of cefaclor extended-release tablets in pediatric patients less than 16 years of age have not been established.

Geriatric Use

Of the 3272 patients in clinical studies of cefaclor extended-release tablets, 608 (18.2%) were 65 and older. No overall differences in safety or effectiveness were observed between these and younger patients. Other reported clinical experience has not identified differences in responses between the elderly and younger patients, but greater sensitivity of some older individuals cannot be ruled out.

This drug is known to be substantially excreted by the kidney (see CLINICAL PHARMACOLOGY), and the risk of toxic reactions to this drug may be greater in patients with impaired renal function. Because elderly patients are more likely to have decreased renal function, care should be taken in dose selection, and it may be useful to monitor renal function (see DOSAGE AND ADMINISTRATION).

ADVERSE REACTIONS

Clinical Trials

There were 3272 patients treated with multiple doses of cefaclor extended-release tablets in controlled clinical trials and an additional 211 subjects in pharmacology studies. There were no deaths in these trials thought to be related to toxicity from cefaclor extended-release tablets. Treatment was discontinued in 1.7% of patients due to adverse events thought to be possibly or probably drug-related.

The following adverse clinical and laboratory events were reported during the cefaclor extended-release tablets clinical trials conducted in North America at doses of 375 mg or 500 mg BID; however, relatedness of the adverse events to the drug was not assigned by clinical investigators during the trials (see TABLES 4 and 5).

Table 4: ADVERSE CLINICAL EVENTS - CEFACLOR EXTENDED-RELEASE TABLETS MULTIPLE DOSE DOSING REGIMENS CLINICAL TRIALS - NORTH AMERICA (n = 1400)
Incidence Equal to or Greater Than 1% | Event | Incidence
Incidence Equal to or Greater Than 1% | Headache | 4.9%
Incidence Equal to or Greater Than 1% | Rhinitis | 3.9%
Incidence Equal to or Greater Than 1% | Diarrhea | 3.8%
Incidence Equal to or Greater Than 1% | Nausea | 3.4%
Incidence Equal to or Greater Than 1% | Vaginitis [n = 934 for these events (subset of female participants).] | 2.4%
Incidence Equal to or Greater Than 1% | Vaginal Moniliasis | 2.2%
Incidence Equal to or Greater Than 1% | Abdominal Pain | 1.6%
Incidence Equal to or Greater Than 1% | Cough Increased | 1.5%
Incidence Equal to or Greater Than 1% | Pharyngitis | 1.4%
Incidence Equal to or Greater Than 1% | Pruritus | 1.4%
Incidence Equal to or Greater Than 1% | Back Pain | 1.0%

Adverse reactions occurring during the clinical trials with cefaclor extended-release tablets with an incidence of less than 1% but greater than 0.1% included the following (listed alphabetically):

Accidental injury, anorexia, anxiety, arthralgia, asthma, bronchitis, chest pain, chills, congestive heart failure, conjunctivitis, constipation, dizziness, dysmenorrhea, dyspepsia, dysuria, ear pain, edema, fever, flatulence, flu syndrome, gastritis, infection, insomnia, leukorrhea, lung disorder, maculopapular rash, malaise, menstrual disorder, myalgia, nausea and vomiting, neck pain, nervousness, nocturia, otitis media, pain, palpitation, peripheral edema, rash, respiratory disorder, sinusitis, somnolence, surgical procedure, sweating, tremor, urticaria, vomiting.

NOTE: One case of serum-sickness-like reaction was reported among the 3272 adult patients treated with cefaclor extended-release tablets during the controlled clinical trials. These reactions have also been reported with the use of cefaclor in other oral formulations and are seen more frequently in pediatric patients than in adults. These reactions are characterized by findings of erythema multiforme, rash, and other skin manifestations accompanied by arthritis/arthralgia, with or without fever, and differ from classic serum sickness in that there is infrequently associated lymphadenopathy and proteinuria, no circulating immune complexes and no evidence to date of sequelae of the reaction. While further investigation is ongoing, serum-sickness-like reactions appear to be due to hypersensitivity and more often occur during or following a second (or subsequent) course of therapy with cefaclor. Such reactions have been reported with overall occurrence ranging from 1 in 200 (0.5%) in one focused trial; to 2 in 8346 (0.024%) in overall clinical trials (with an incidence in pediatric patients in clinical trials of 0.055%); to 1 in 38,000 (0.003%) in spontaneous event reports. Signs and symptoms usually occur a few days after initiation of therapy and subside within a few days after cessation of therapy. Occasionally these reactions have resulted in hospitalization, usually of short duration (median hospitalization = 2 to 3 days, based on postmarketing surveillance studies). In those patients requiring hospitalization, the symptoms have ranged from mild to severe at the time of admission with more of the severe reactions occurring in pediatric patients.

Table 5: ADVERSE CLINICAL LABORATORY EVENTS CEFACLOR EXTENDED-RELEASE TABLETS MULTIPLE DOSE DOSING REGIMENS CLINICAL TRIALS – NORTH AMERICA
 | Event | Incidence
Incidence Less Than 1%, but Greater Than 0.1% | Albumin decreased | 0.3%
Incidence Less Than 1%, but Greater Than 0.1% | Alkaline phosphatase increased | 0.3%
Incidence Less Than 1%, but Greater Than 0.1% | ALT/SGPT increased | 0.3%
Incidence Less Than 1%, but Greater Than 0.1% | Bilirubin total increased | 0.3%
Incidence Less Than 1%, but Greater Than 0.1% | Blood urea nitrogen (BUN) increased | 0.2%
Incidence Less Than 1%, but Greater Than 0.1% | Calcium decreased | 0.7%
Incidence Less Than 1%, but Greater Than 0.1% | Creatine phosphokinase increased | 0.7%
Incidence Less Than 1%, but Greater Than 0.1% | Creatinine increased | 0.5%
Incidence Less Than 1%, but Greater Than 0.1% | Eosinophils increased | 0.3%
Incidence Less Than 1%, but Greater Than 0.1% | Erythrocyte count decreased | 0.3%
Incidence Less Than 1%, but Greater Than 0.1% | GGT increased | 0.2%
Incidence Less Than 1%, but Greater Than 0.1% | Hemoglobin decreased | 0.2%
Incidence Less Than 1%, but Greater Than 0.1% | Lymphocytes decreased | 0.3%
Incidence Less Than 1%, but Greater Than 0.1% | Mean Cell Volume (MCV) increased | 0.7%
Incidence Less Than 1%, but Greater Than 0.1% | Neutrophils segmented decreased | 0.3%
Incidence Less Than 1%, but Greater Than 0.1% | Phosphorous increased | 0.7%
Incidence Less Than 1%, but Greater Than 0.1% | Platelet count decreased | 0.3%
Incidence Less Than 1%, but Greater Than 0.1% | Potassium increased | 0.4%
Incidence Less Than 1%, but Greater Than 0.1% | Sodium decreased | 0.3%
Incidence Less Than 1%, but Greater Than 0.1% | Sodium increased | 0.4%

In Postmarketing Experience

In addition to the events reported during clinical trials with cefaclor extended-release tablets, the following adverse experiences are among those that have been reported during worldwide postmarketing surveillance: allergic reaction, anaphylactoid reaction, angioedema, face edema, hypotension, Stevens-Johnson syndrome, syncope, paresthesia, vasodilatation and vertigo.

Other Adverse Reactions Associated With Other Formulations of Cefaclor

In addition to the above, the following other adverse reactions and altered laboratory tests have been associated with cefaclor in other oral formulations:

Clinical

Severe hypersensitivity reactions, including Stevens-Johnson syndrome, toxic epidermal necrolysis, and anaphylaxis, have been reported rarely. Anaphylactoid events may be manifested by solitary symptoms, including angioedema, edema (including face and limbs), paresthesias, syncope, or vasodilatation. Anaphylaxis may be more common in patients with a history of penicillin allergy. Rarely, hypersensitivity symptoms may persist for several months.

Symptoms of pseudomembranous colitis may appear either during or after antibiotic treatment. (See WARNINGS.)

Laboratory

Abnormal urinalysis, eosinophilia, leukopenia, neutropenia, transient elevations in AST, and transient thrombocytopenia have been reported.

Cephalosporin-Class Reactions

In addition to the adverse reactions listed above, the following adverse reactions and altered laboratory tests have been reported for cephalosporin-class antibiotics:

Clinical

Confusion, erythema multiforme, genital pruritus, hepatic dysfunction including cholestasis, hemolytic anemia, reversible hyperactivity, hypertonia, and reversible interstitial nephritis.

Laboratory

Positive direct Coombs’ test.

OVERDOSAGE

The toxic symptoms following an overdose of cefaclor may include nausea, vomiting, epigastric distress, and diarrhea. The severity of the epigastric distress and the diarrhea are dose-related.

Absorption of drugs from the gastrointestinal tract may be decreased by giving activated charcoal, which, in many cases, is more effective than emesis or lavage. Consider charcoal instead of or in addition to gastric emptying. Repeated doses of charcoal over time may hasten elimination of some drugs that have been absorbed.

Although cefaclor is considered dialyzable, neither forced diuresis, peritoneal dialysis, hemodialysis, nor charcoal hemoperfusion have been demonstrated to be beneficial in an overdose of cefaclor.

DOSAGE AND ADMINISTRATION

The absorption of cefaclor extended-release tablets is enhanced when it is administered with food. (See CLINICAL PHARMACOLOGY.) Therefore, cefaclor extended-release tablets should be administered with meals (i.e., at least within one hour of eating). The extended-release tablets should not be cut, crushed, or chewed.

See INDICATIONS AND USAGE for information about patients for whom cefaclor extended-release tablets are indicated.

NOTE: 500 mg BID of cefaclor extended-release tablets is clinically equivalent to 250 mg TID of cefaclor immediate-release as a capsule in those indications listed in the INDICATIONS AND USAGE section of this label. 500 mg BID of cefaclor extended-release tablets is NOT equivalent to 500 mg TID of other cefaclor formulations.

Adults (age 16 years and older):

Type of Infection (as qualified in the INDICATIONS AND USAGE section of this labeling) | Total Daily Dose | Dose and Frequency | Duration
Acute Bacterial Exacerbations of Chronic Bronchitis due to H. influenzae (non-ß-lactamase-producing strains only). Moraxella catarrhalis (including ß-lactamase-producing strains), or Streptococcus pneumoniae (See INDICATIONS AND USAGE.) | 1000 mg | 500 mg q 12 hours | 7 days
Pharyngitis and/or tonsillitis due to S. pyogenes | 750 mg | 375 mg q 12 hours | 10 days
Uncomplicated Skin and Skin Structure Infections due to S. aureus (methicillin-susceptible strains) (See INDICATIONS AND USAGE.) | 750 mg | 375 mg q 12 hours | 7 to 10 days

Elderly patients with normal renal function do not require dosage adjustments.

HOW SUPPLIED

Cefaclor Extended-release Tablets USP, 500 mg (based on the anhydrous), are available as film-coated, oval-shaped, unscored, dark blue tablets, debossed with “93” on one side and “1087” on the other side. They are available in bottles of 100. (NDC 0093-1087-01)

Store at 20° to 25°C (68° to 77°F) [See USP Controlled Room Temperature].

Dispense in a tight, light-resistant container as defined in the USP, with a child-resistant closure (as required).

CLINICAL STUDIES

ACUTE BACTERIAL EXACERBATIONS OF CHRONIC BRONCHITIS

In adequate and well-controlled clinical trials of cefaclor extended-release tablets in the treatment of acute bacterial exacerbations of chronic bronchitis (ABECB), only 4 evaluable patients with ABECB had infections caused by ß-lactamase-producing H. influenzae. Four patients do not provide adequate data upon which to judge clinical efficacy of cefaclor extended-release tablets against ß-lactamase-producing H. influenzae.

UNCOMPLICATED SKIN AND SKIN STRUCTURE INFECTIONS

Cefaclor extended-release tablets (375 mg Q12H) (n = 115) were compared to cefaclor immediate-release capsules (250 mg TID) (n = 106) for the treatment of patients with uncomplicated skin and skin structure infections, including cellulitis, pyoderma, abscess and impetigo. Patients were treated for 7 to 10 days and were evaluated for clinical resolution and bacterial eradication approximately one week after completing therapy. To be evaluable, all patients had to have a recognized pathogen isolated from the skin infection just prior to the initiation of therapy. The results of this randomized, double-blinded, U.S. trial demonstrated:

1. overall clinical cure rates were 72% (83 of 115 patients) and 75% (80 of 106 patients), respectively, for cefaclor extended-release tablets and cefaclor immediate-release capsules [95% CI around the 3% difference = -16% to +9%],
2. overall bacteriologic eradication rates against Staphylococcus aureus were comparable (see TABLE 6).

Table 6: CLINICAL RESPONSE [Cure plus improvement] IN PATIENTS WITH SKIN AND SKIN STRUCTURE INFECTIONS
Outcome by Pathogen | CEFACLOR EXTENDED-RELEASE TABLETS |  | CEFACLOR IMMEDIATE-RELEASE CAPSULES
Staphylococcus aureus | 67/95 | (71%) | 58/81 | (71%)
Streptococcus pyogenes | 10/16 | (63%) | 8/9 | (89%)
Other streptococci | 7/11 | (64%) | 5/6 | (83%)
Total | 84/122 | (69%) | 71/96 | (74%)

All brand names listed are the registered trademarks of their respective owners and are not trademarks of Teva Pharmaceuticals USA.

Teva Pharmaceuticals USA, Inc.

North Wales, PA 19454

Rev. N 7/2019

Package/Label Display Panel

NDC 0093-1087-01

Cefaclor

Extended-Release

Tablets USP

500 mg

Rx only

100 TABLETS

TEVA